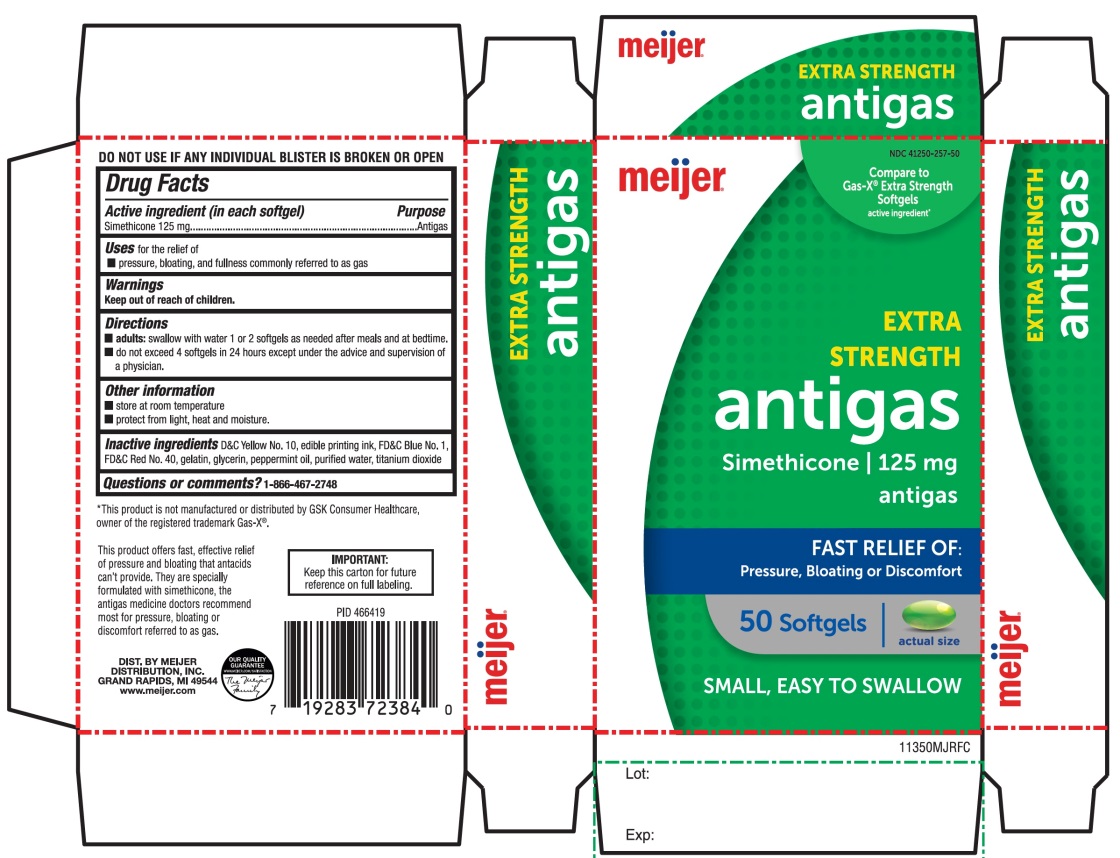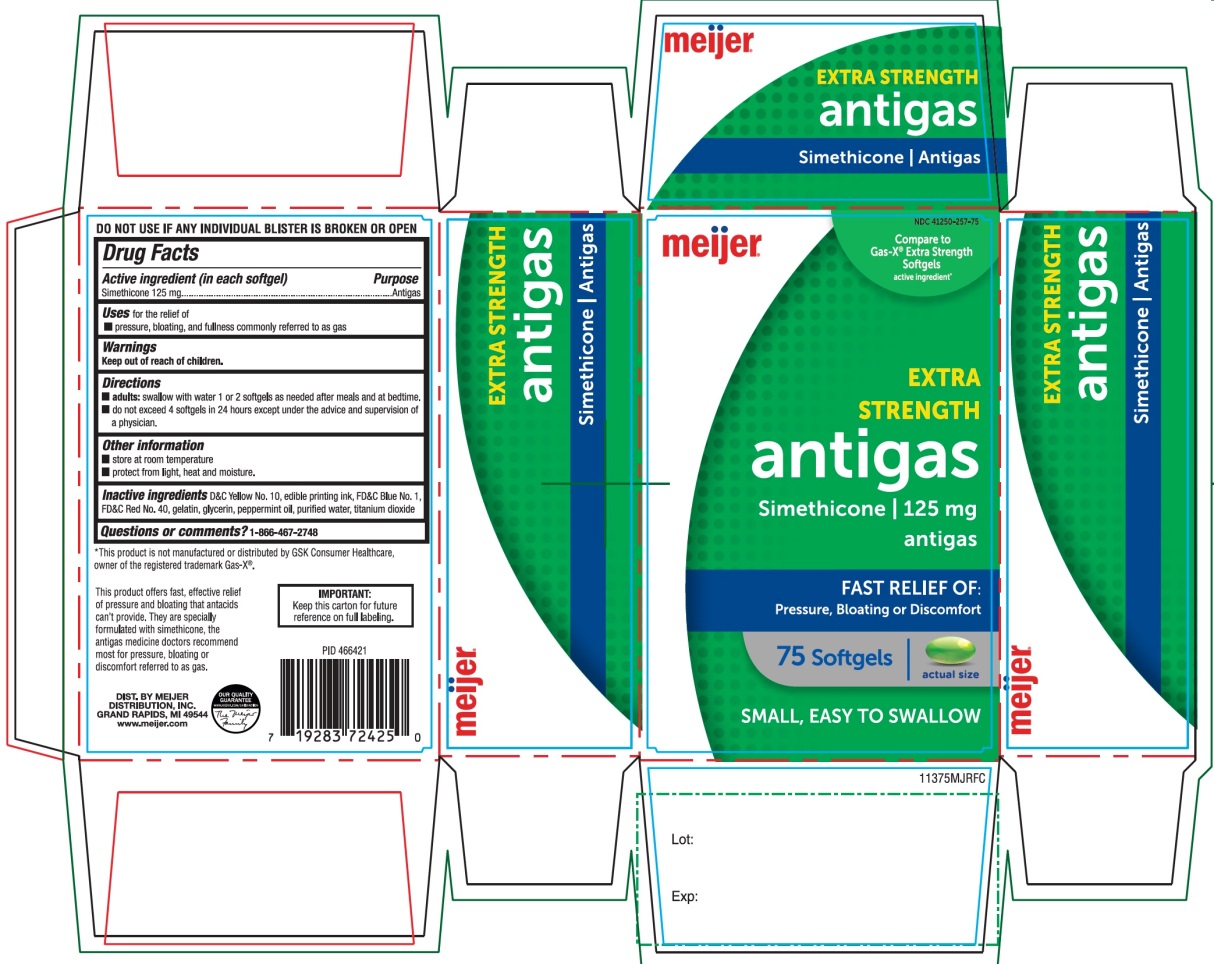 DRUG LABEL: Meijer Extra Strength

NDC: 41250-257 | Form: CAPSULE, LIQUID FILLED
Manufacturer: MEIJER DISTRIBUTION INC
Category: otc | Type: HUMAN OTC DRUG LABEL
Date: 20251024

ACTIVE INGREDIENTS: DIMETHICONE, UNSPECIFIED 125 mg/1 1
INACTIVE INGREDIENTS: D&C YELLOW NO. 10; FD&C BLUE NO. 1; FD&C RED NO. 40; GELATIN, UNSPECIFIED; GLYCERIN; PEPPERMINT OIL; WATER; TITANIUM DIOXIDE

Extra Strength Gas Relief Simethicone 125mg Antigas

Active ingredient (in each softgel)

Simethicone 125 mg

Purpose

Antigas

Uses for the relief

- pressure, bloating, and fullness commonly referred to as gas

Directions

- adults: swallow with water 1 or 2 softgels as needed after meals and at bedtime.
- do not exceed 4 softgels in 24 hours except under the advice and supervision of a physician

Other information

- store at room temperature
- protect from light, heat, and moisture

Inactive ingredients

D&C Yellow No. 10, edible printing ink, FD&C Blue No.1, FD&C Red No. 40, gelatin, glycerin, peppermint oil, purified water, titanium dioxide

Questions or comments?

1-866-467-2748

Principal Display Panel

*Compare to active ingredient in Gas-X® Extra Strength Softgels active ingredient*

EXTRA STRENGTH

antigas

Simethicone/125 mg Antigas

FOR FAST RELIEF OF:

- Pressure
- Bloating
- Discomfort

DO NOT USE IF BLISTER UNIT IS BROKEN OR OPEN

IMPORTANT:Keep this carton for future reference on full labeling

*This product is not manufactured or distributed by GSK Consumer Healthcare, Inc. the distributor of Gas-X®.

DIST. BY

MEIJER DISTRIBUTION INC,

GRAND RAPIDS, MI 49544

www.meijer.com

OUR QUALITY GUARANTEE

This product offers fast, effective relief of pressure and bloating that antacids can’t provide.

They are specially formulated with simethicone, the antigas medicine doctors recommends most for pressure, bloating or discomfort referred to as gas.

Package Label for Extra Strength Gas Relief 50 Softgels